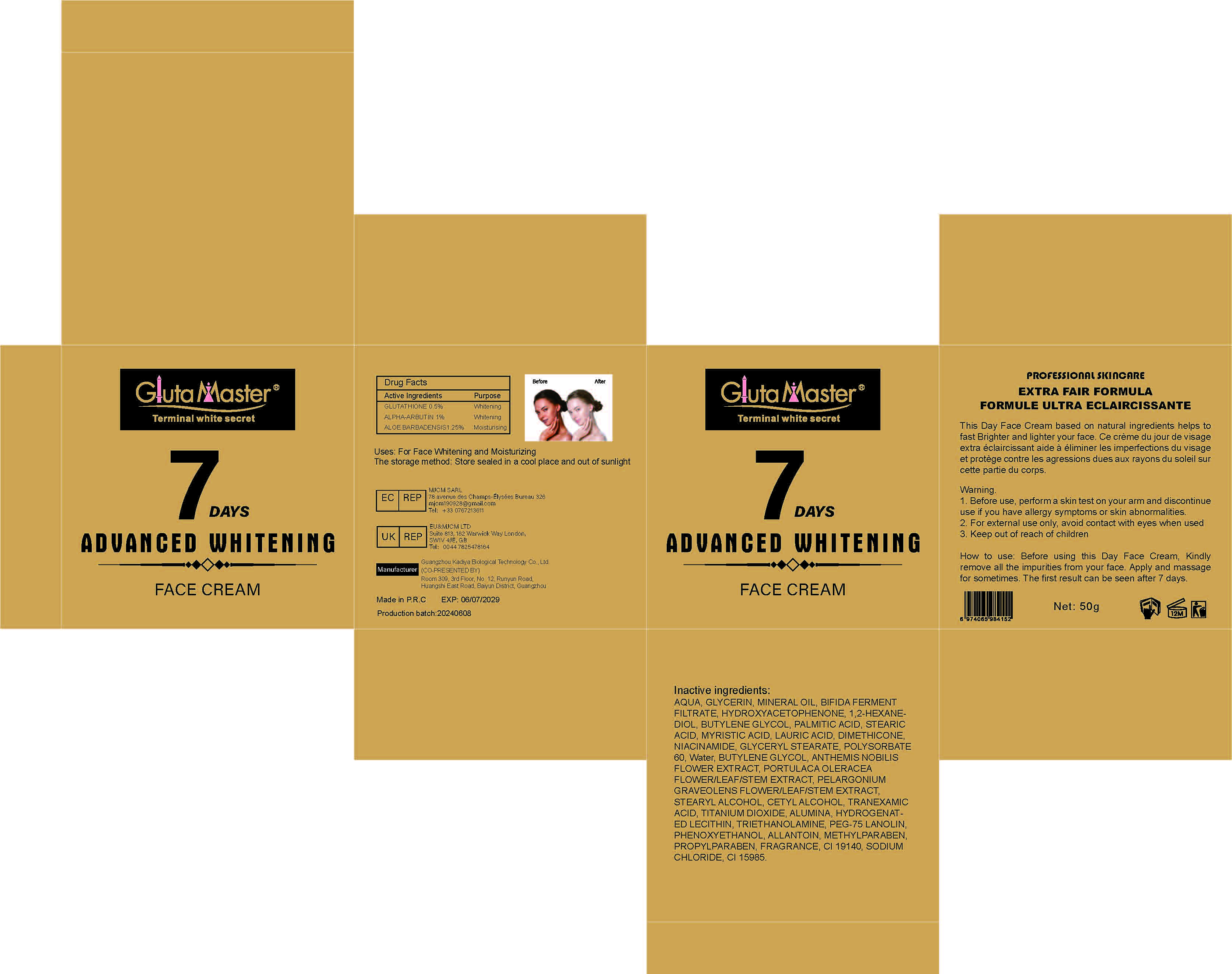 DRUG LABEL: 7 Days Whitening Face Cream
NDC: 84423-006 | Form: CREAM
Manufacturer: Guangzhou Kadiya Biotechnology Co.,,Ltd.
Category: otc | Type: HUMAN OTC DRUG LABEL
Date: 20240628

ACTIVE INGREDIENTS: ALPHA-ARBUTIN 0.5 mg/50 mg; GLUTATHIONE 0.25 mg/50 mg; ALOE VERA LEAF 0.625 mg/50 mg
INACTIVE INGREDIENTS: TROLAMINE; PHENOXYETHANOL; FD&C YELLOW NO. 5; WATER; DIMETHICONE; CHAMAEMELUM NOBILE FLOWER; PELARGONIUM GRAVEOLENS FLOWERING TOP; SODIUM CHLORIDE; GLYCERYL MONOSTEARATE; ALUMINUM OXIDE; PALMITIC ACID; FD&C YELLOW NO. 6; GLYCERIN; BUTYLENE GLYCOL; TITANIUM DIOXIDE; 1,2-HEXANEDIOL; HYDROXYACETOPHENONE; NIACINAMIDE; STEARYL ALCOHOL; CETYL ALCOHOL; LAURIC ACID; ALLANTOIN; PROPYLPARABEN; TRANEXAMIC ACID; MINERAL OIL; PURSLANE; PEG-75 LANOLIN; METHYLPARABEN; STEARIC ACID; MYRISTIC ACID; POLYSORBATE 60

ACTIVE INGEDIENT

GLUTATHIONE 0.5%
ALPHA-ARBUTIN 1%
ALOE BARBADENSIS1.25%

PURPOSE

For Face Whitening and Hydrating

INACTIVE INGREDIENT

AQUA, GLYCERIN, MINERAL OIL, HYDROXYACETOPHENONE, 1,2-HEXANEDIOL,BUTYLENE GLYCOL, PALMITIC ACID, STEARIC ACID, MYRISTIC ACID, LAURIC ACID, DIMETHICONE, NIACINAMIDE, GLYCERYL STEARATE, POLYSORBATE 60, Water, BUTYLENE GLYCOL, ANTHEMIS NOBILIS FLOWER EXTRACT, PORTULACA OLERACEA FLOWER/LEAF/STEM EXTRACT, PELARGONIUM GRAVEOLENS FLOWER/LEAF/STEM EXTRACT, STEARYL ALCOHOL, CETYL ALCOHOL, TRANEXAMIC ACID, TITANIUM DIOXIDE, ALUMINA, TRIETHANOLAMINE, PEG-75 LANOLIN, PHENOXYETHANOL, ALLANTOIN, METHYLPARABEN, PROPYLPARABEN, CI 19140, SODIUM CHLORIDE, CI 15985.

WARNING

1. Before use, perform a skin test on your arm and discontinue
use if you have allergy symptoms or skin abnormalities.
2. For external use only, avoid contact with eyes when used
3. Keep out of reach of children

INSTRUCTIONS FOR USE

Before using this Day Face Cream, Kindly remove all the impurities from your face. Apply and massage for sometimes.

INDICATIONS

Before using this Day Face Cream, Kindly remove all the impurities from your face. Apply and massage for sometimes. The first result can be seen after 7 days.

DOSAGE

For external use only, avoid contact with eyes when used

WARNING

keep out of reach of children

PACKAGE LABEL

7 DAYS WHITENING FACE CREAM

1. Active Ingredients
GLUTATHIONE 0.5%
ALPHA-ARBUTIN 1%
ALOE BARBADENSIS1.25%

2.Purpose
For Face Whitening and Moisturizing

3.Inactive ingredients:
AQUA, GLYCERIN, MINERAL OIL, HYDROXYACETOPHENONE, 1,2-HEXANEDIOL,BUTYLENE GLYCOL, PALMITIC ACID, STEARIC ACID, MYRISTIC ACID, LAURIC ACID, DIMETHICONE, NIACINAMIDE, GLYCERYL STEARATE, POLYSORBATE 60, Water, BUTYLENE GLYCOL, ANTHEMIS NOBILIS FLOWER EXTRACT, PORTULACA OLERACEA FLOWER/LEAF/STEM EXTRACT, PELARGONIUM GRAVEOLENS FLOWER/LEAF/STEM EXTRACT, STEARYL ALCOHOL, CETYL ALCOHOL, TRANEXAMIC ACID, TITANIUM DIOXIDE, ALUMINA, TRIETHANOLAMINE, PEG-75 LANOLIN, PHENOXYETHANOL, ALLANTOIN, METHYLPARABEN, PROPYLPARABEN, CI 19140, SODIUM CHLORIDE, CI 15985.

4.Warning
1. Before use, perform a skin test on your arm and discontinue use if you have allergy symptoms or skin abnormalities.
2. For external use only, avoid contact with eyes when used
3. Keep out of reach of children